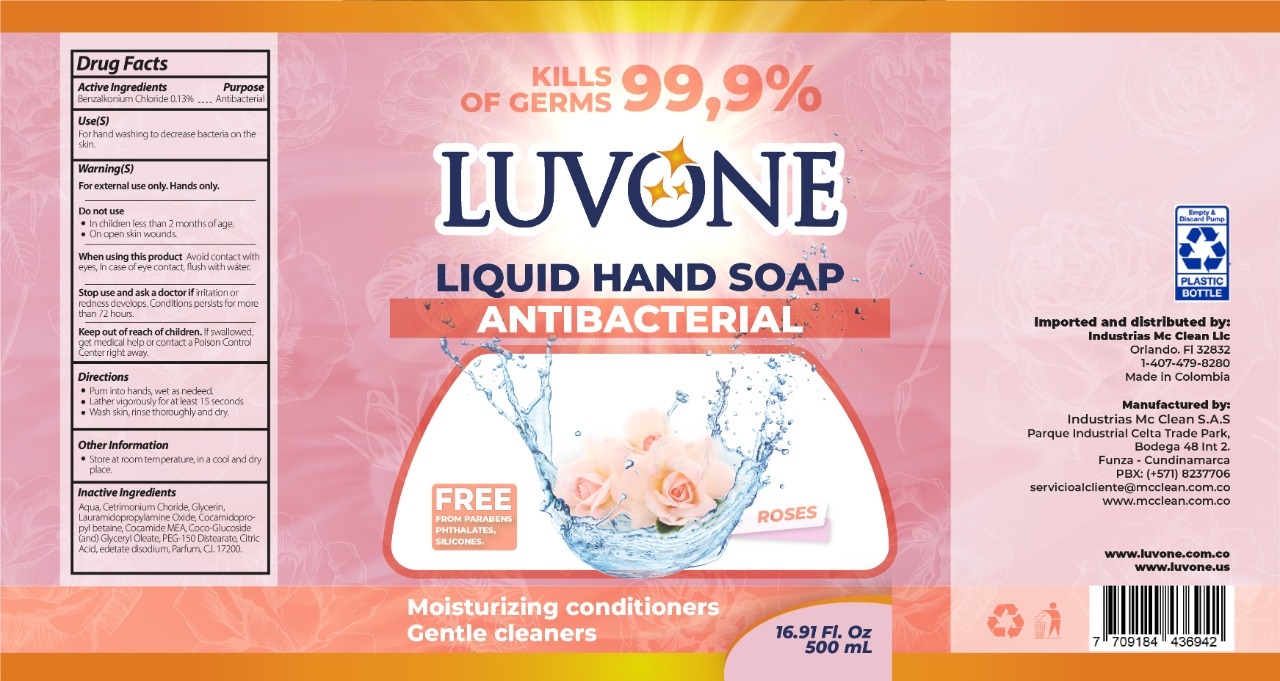 DRUG LABEL: Luvone Hand antibacterial Roses
NDC: 80683-005 | Form: LIQUID
Manufacturer: INDUSTRIAS MC CLEAN S A S
Category: otc | Type: HUMAN OTC DRUG LABEL
Date: 20210714

ACTIVE INGREDIENTS: BENZALKONIUM CHLORIDE 1.3 mg/1 mL
INACTIVE INGREDIENTS: WATER; CETRIMONIUM CHLORIDE; GLYCERIN; LAURAMIDOPROPYLAMINE OXIDE; COCAMIDOPROPYL BETAINE; COCO MONOETHANOLAMIDE; COCO GLUCOSIDE; GLYCERYL OLEATE; PEG-150 DISTEARATE; CITRIC ACID MONOHYDRATE; EDETATE DISODIUM; D&C RED NO. 33

Luvone liquid Hand soap antibacterial Roses

Active Ingredients

Benzalkonium Chlorie 0.13%

Purpose

Antibacterial

Use(S)

For hand washing to decrease bacteria on the skin.

Warning(S)

For external use only. Hands only.

Do not use

- In children less than 2 months of age.
- On open skin wounds.

When using this product

Avoid contact with eyes. In case of eye contact, flush with water.

Stop use and ask a doctor if

irritation or redness develops. Conditions persists for more than 72 hours.

Keep out of reach of children.

If swallowed, get medical help or contact a Poison Control Center right away.

Directions

- Pum into hands, wet as nedeed.
- Lather vigorously for at least 15 seconds
- Wash skin, rinse thoroughly and dry.

Other Information

- Store at room temperature, in a cool and dry place.

Inactive Ingredients

Aqua, Cetrimonium Choride, Glycerin, Lauramidopropylamine Oxide, Cocamidopropyl betaine, Cocoamido MEA, Coco-Glucoside (and) Glyceryl Oleate, PEG-150 Distearate, Citric Acid, edetate disodium, Parfum, CI 17200.